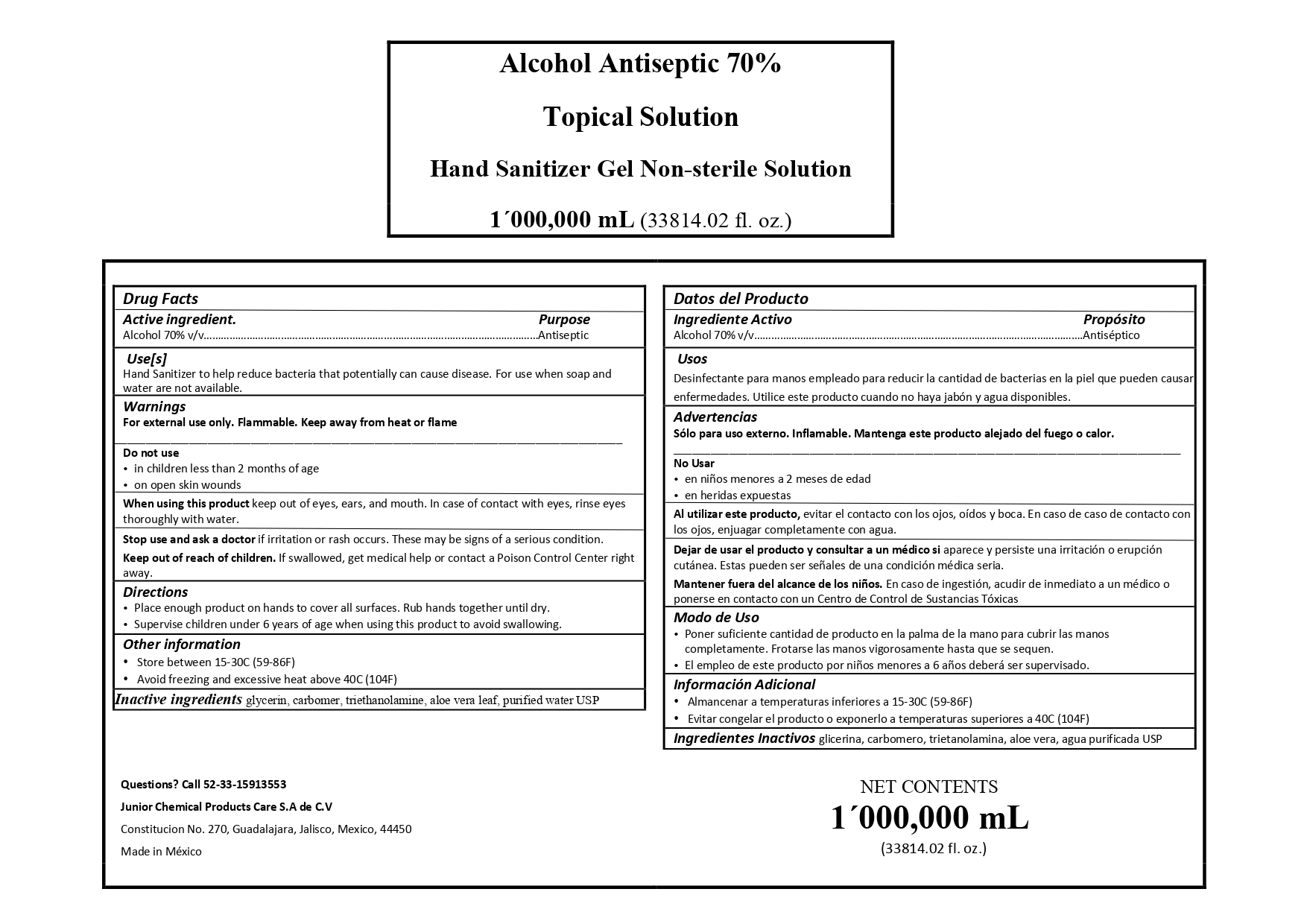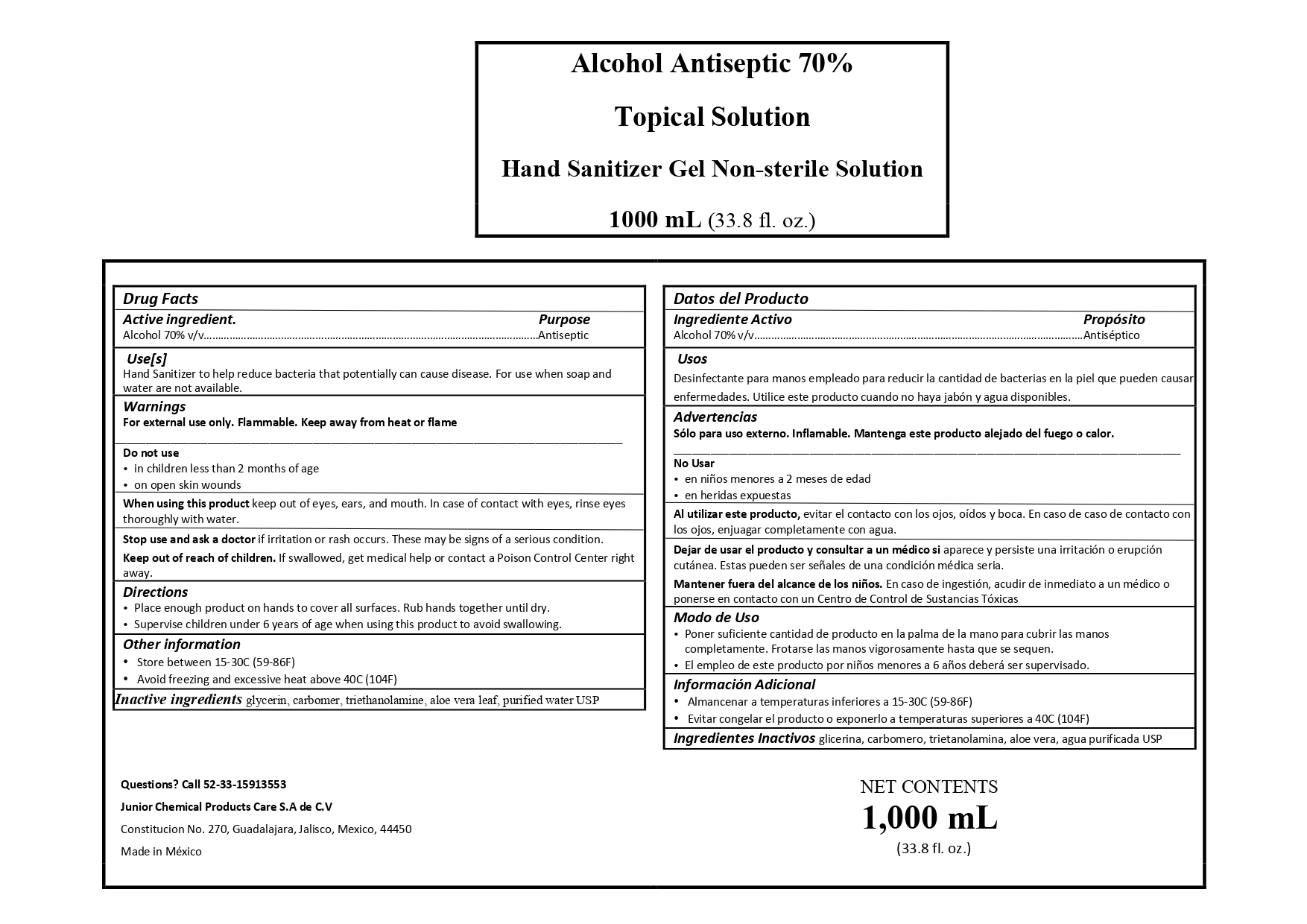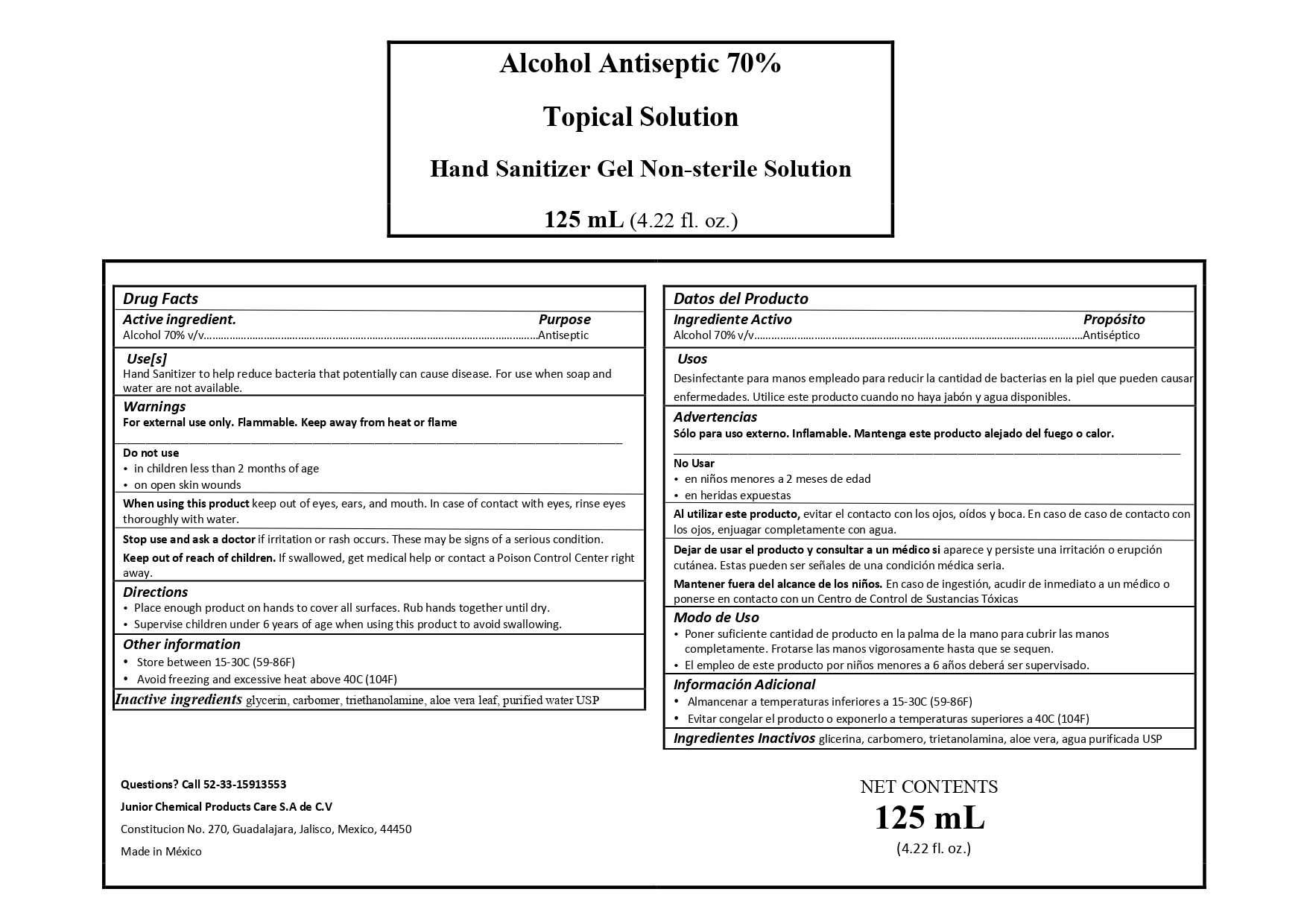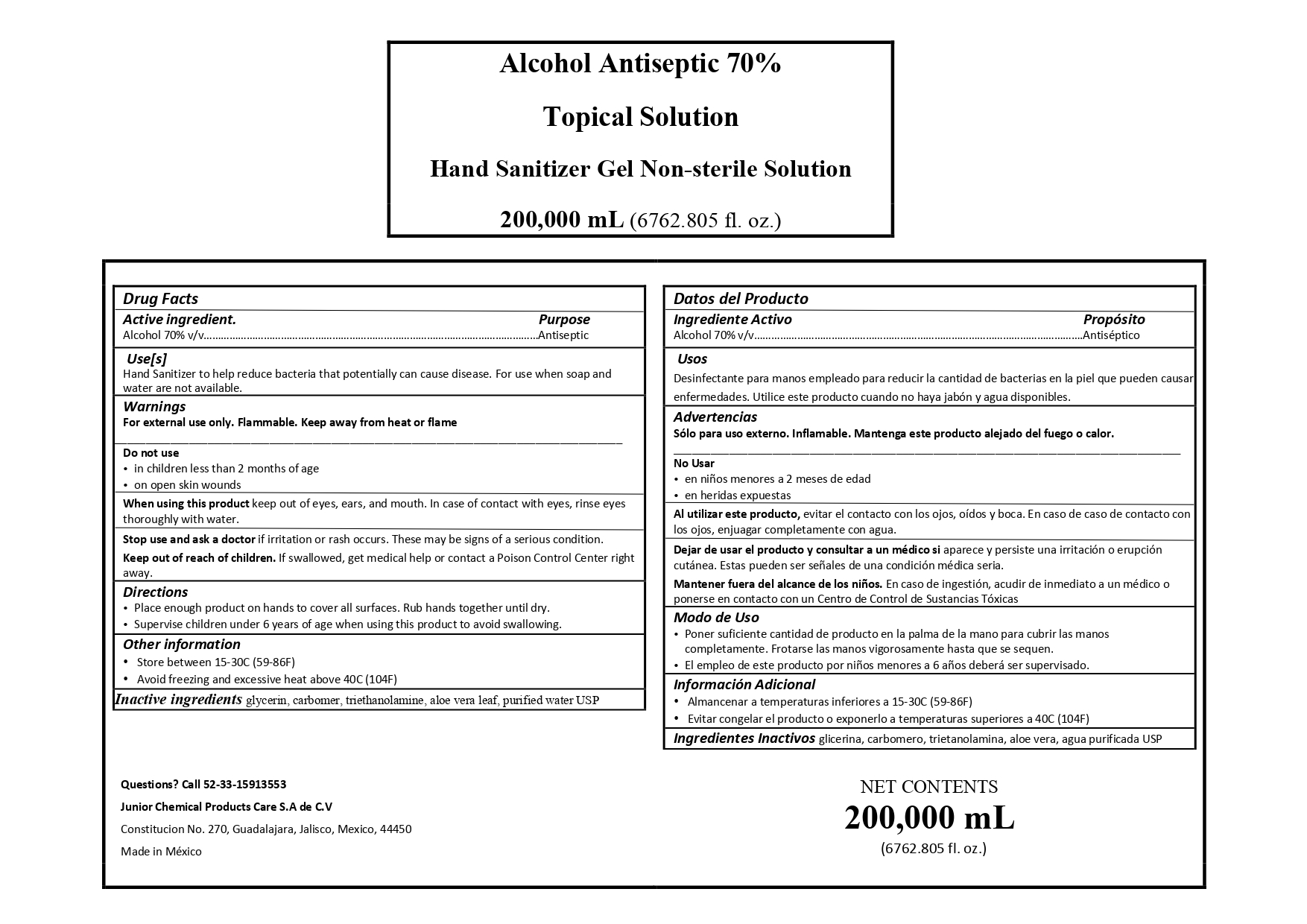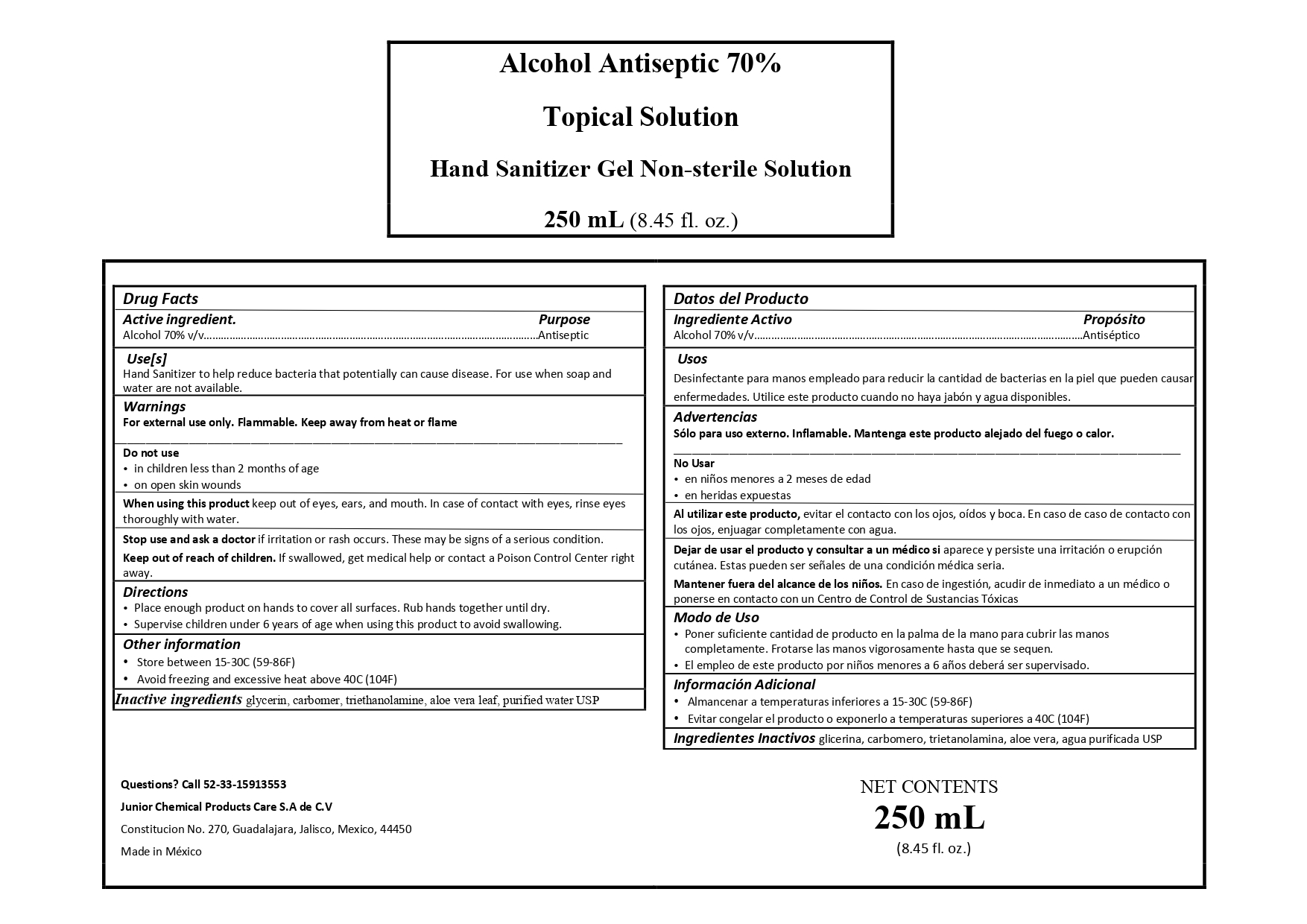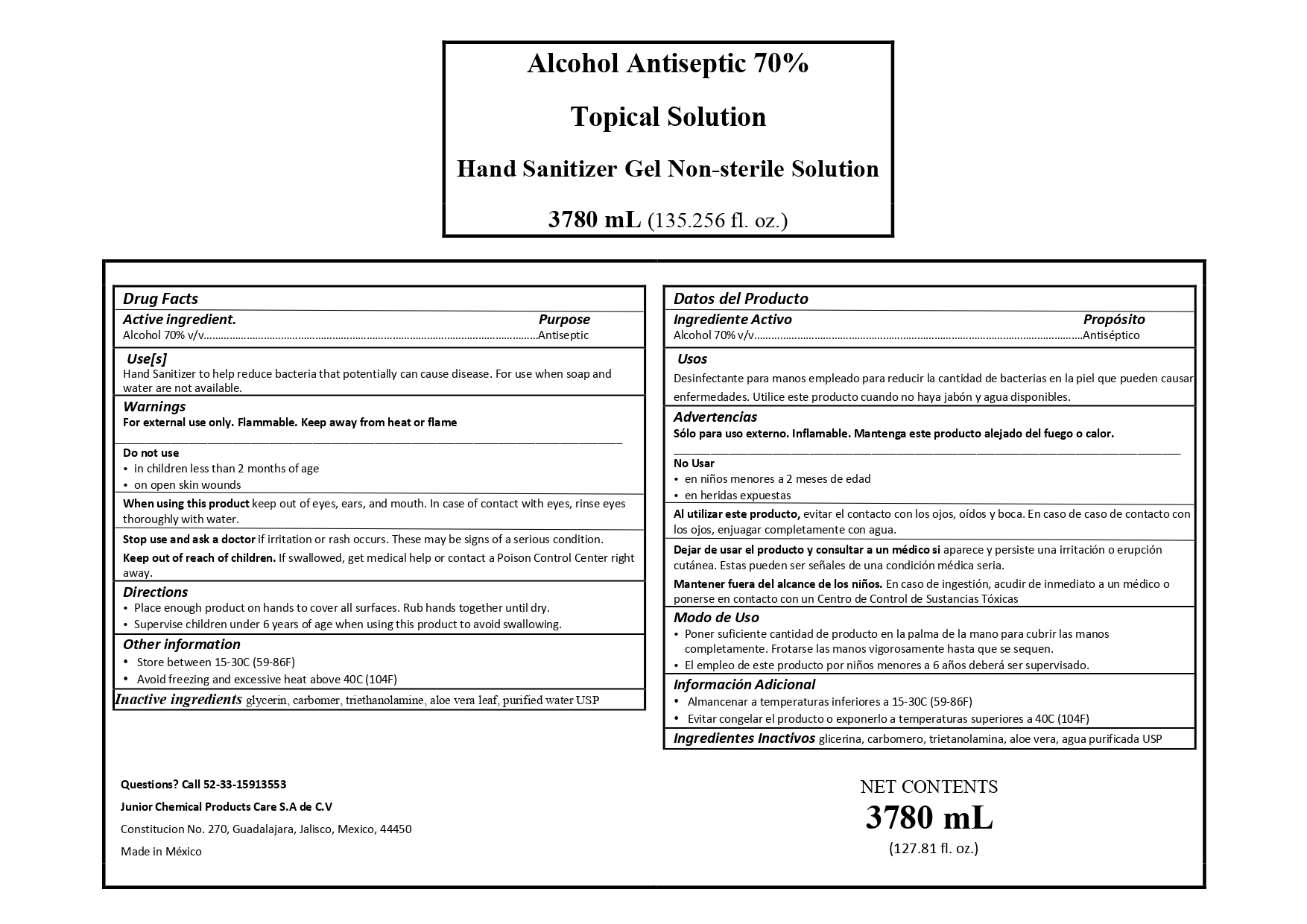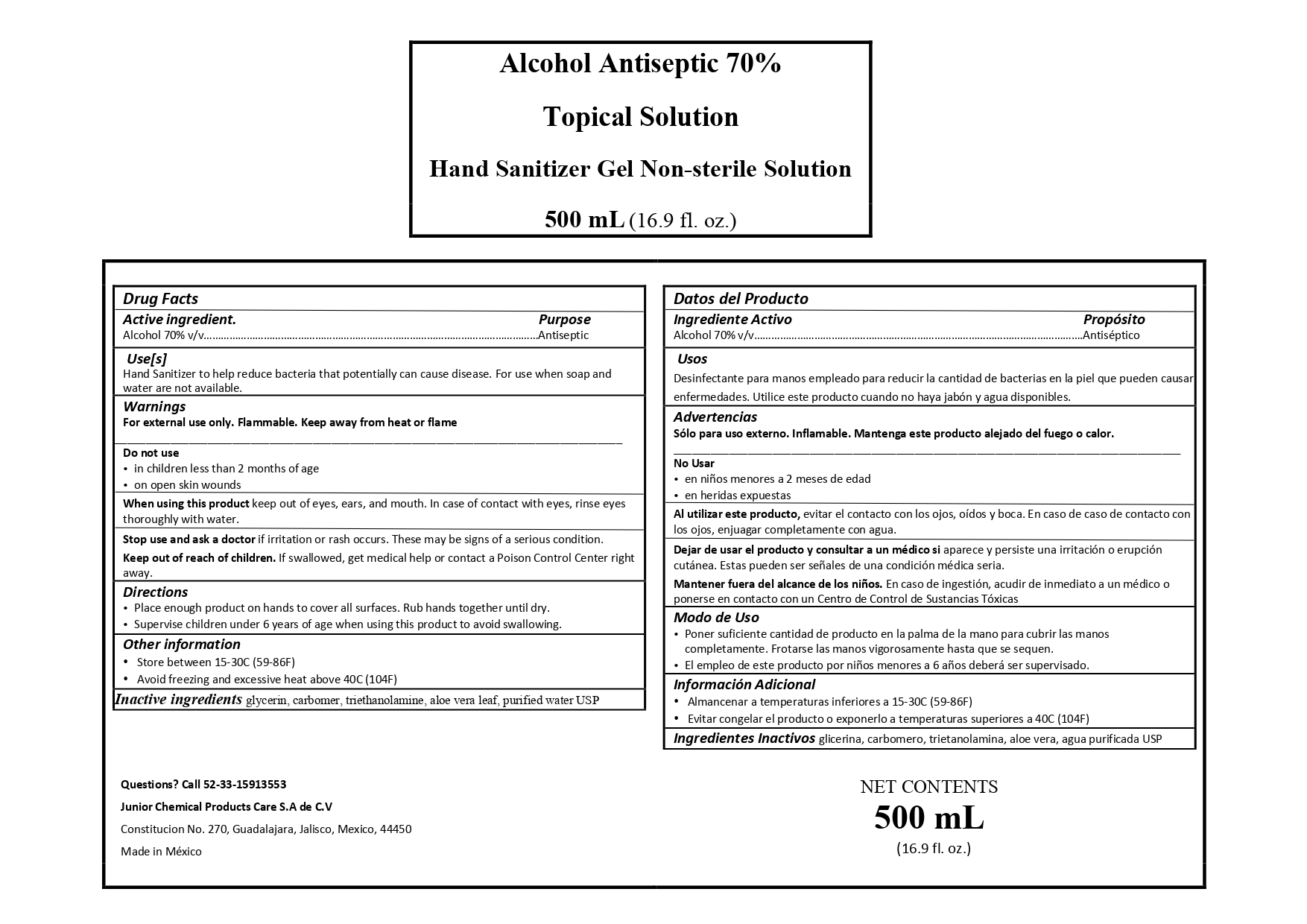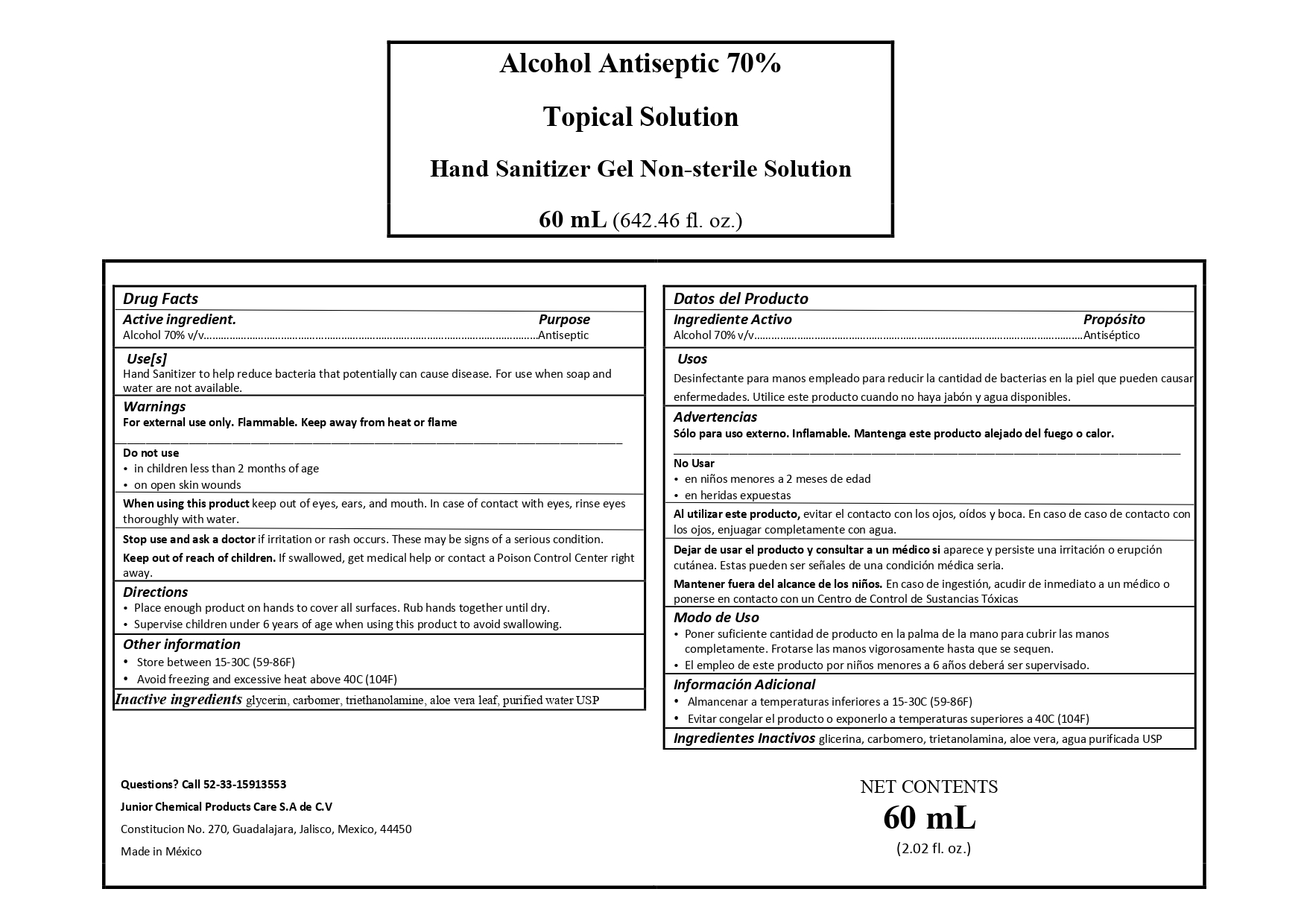 DRUG LABEL: Hand Sanitizer
NDC: 78359-001 | Form: GEL
Manufacturer: Junior Chemical Products Care S.A. de C.V.
Category: otc | Type: HUMAN OTC DRUG LABEL
Date: 20200525

ACTIVE INGREDIENTS: ALCOHOL 70 mL/100 mL
INACTIVE INGREDIENTS: GLYCERIN 1.45 mL/100 mL; WATER; TRIETHANOLAMINE CAPROYL GLUTAMATE 0.12 mL/100 mL; CARBOMER 980 0.86 mL/100 mL; ALOE VERA LEAF POLYSACCHARIDES 0.2 mL/100 mL

Hand Sanitizer

The hand sanitizer is manufactured using only the following United States Pharmacopoeia (USP) grade ingredients in the preparation of the product (percentage in final product formulation) consistent with World Health Organization (WHO) recommendations:

Alcohol (ethanol) (USP or Food Chemical Codex (FCC) grade) (70%, volume/volume (v/v)) in an aqueous solution denatured according to Alcohol and Tobacco Tax and Trade Bureau regulations in 27 CFR part 20.

Glycerin (1.45% v/v).

Triethanolamine capryol glutamate (0.12% v/v).

Sterile distilled water or boiled cold water.

Carbomer 980 (0.86% v/v)

Aloe vera leaf (0.02% v/v)

The firm does not add other active or inactive ingredients. Different or additional ingredients may impact the quality and potency of the product.

Active Ingredient(s)

Alcohol 70% v/v. Purpose: Antiseptic

Purpose

Antiseptic, Hand Sanitizer

When using this product keep out of eyes, ears, and mouth. In case of contact with eyes, rinse eyes thoroughly with water.
Stop use and ask a doctor if irritation or rash occurs. These may be signs of a serious condition.
Keep out of reach of children. If swallowed, get medical help or contact a Poison Control Center right away.

Use

Hand Sanitizer to help reduce bacteria that potentially can cause disease. For use when soap and water are not available.

Stop use and ask a doctor if irritation or rash occurs. These may be signs of a serious condition.

Warnings

For external use only. Flammable. Keep away from heat or flame

Do not use

- in children less than 2 months of age
- on open skin wounds

Keep out of reach of children. If swallowed, get medical help or contact a Poison Control Center right away.

Other information

- Store between 15-30C (59-86F)
- Avoid freezing and excessive heat above 40C (104F)

Inactive ingredients

glycerin, carbomer, triethanolamine caproyl glutamato, aloe vera leaf, purified water USP

Directions

- Place enough product on hands to cover all surfaces. Rub hands together until dry.
- Supervise children under 6 years of age when using this product to avoid swallowing.

Package Label - Principal Display Panel

1000000 mL NDC 78359-001-08